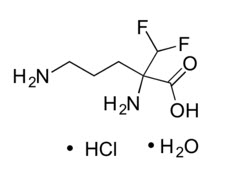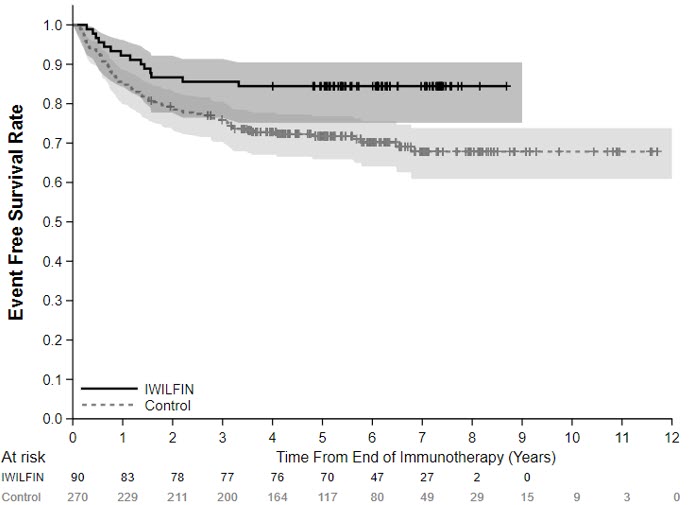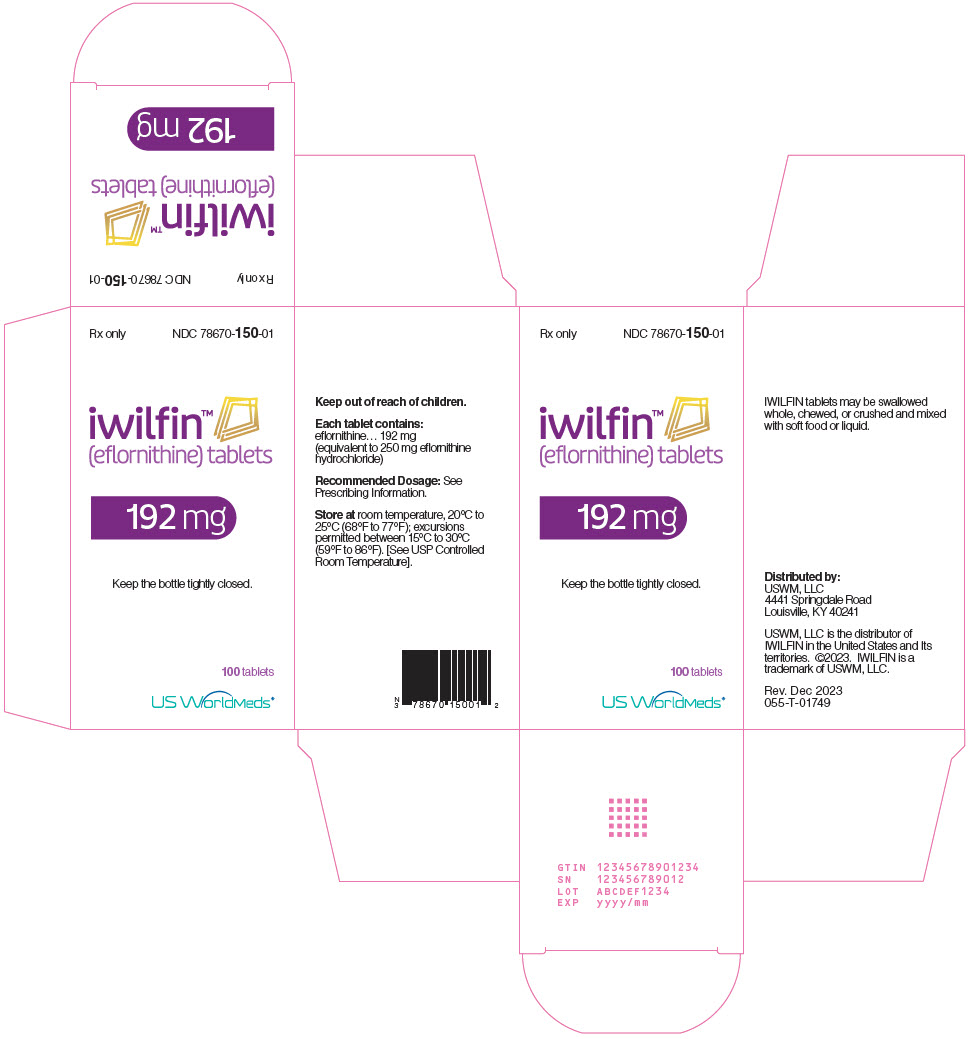 DRUG LABEL: iwilfin
NDC: 78670-150 | Form: TABLET
Manufacturer: USWM, LLC
Category: prescription | Type: HUMAN PRESCRIPTION DRUG LABEL
Date: 20241213

ACTIVE INGREDIENTS: EFLORNITHINE HYDROCHLORIDE 250 mg/1 1
INACTIVE INGREDIENTS: microcrystalline cellulose; silicon dioxide; magnesium stearate

HIGHLIGHTS OF PRESCRIBING INFORMATION

These highlights do not include all the information needed to use IWILFIN® safely and effectively. See full prescribing information for IWILFIN.
IWILFIN® (eflornithine) tablets, for oral use
Initial U.S. Approval: 2023

RECENT MAJOR CHANGES

Dosage and Administration (2.3) | 11/2024

1 INDICATIONS AND USAGE

IWILFIN is an ornithine decarboxylase inhibitor indicated to reduce the risk of relapse in adult and pediatric patients with high-risk neuroblastoma (HRNB) who have demonstrated at least a partial response to prior multiagent, multimodality therapy including anti-GD2 immunotherapy. (1)

2 DOSAGE AND ADMINISTRATION

- Prior to initiation of IWILFIN, perform baseline audiogram, complete blood count, and liver function tests. (2.1, 5.3)
- Recommended dosage of IWILFIN is based on body surface area (see Table 1). (2.2)
- IWILFIN is taken orally twice daily with or without food until disease progression, unacceptable toxicity, or for a maximum of two years. (2.2)
- IWILFIN tablets may be swallowed whole, chewed, or crushed and mixed with soft food or liquid. (2.5)

3 DOSAGE FORMS AND STRENGTHS

Tablets: 192 mg (3)

4 CONTRAINDICATIONS

None (4)

5 WARNINGS AND PRECAUTIONS

- Myelosuppression: Monitor blood counts before and during treatment with IWILFIN. Withhold, reduce dose, or permanently discontinue based on severity. (5.1)
- Hepatotoxicity: Monitor liver function tests before and during treatment with IWILFIN. Withhold, reduce dose, or permanently discontinue based on severity. (5.2)
- Hearing Loss: Monitor hearing before and during treatment with IWILFIN. Withhold, reduce dose, or permanently discontinue based on severity. (5.3)
- Embryo-Fetal Toxicity: Can cause fetal harm. Advise females of reproductive potential of the potential risk to a fetus and to use effective contraception. (5.4, 8.1, 8.3)

6 ADVERSE REACTIONS

- Most common adverse reactions (incidence ≥5%) are hearing loss, otitis media, pyrexia, pneumonia, and diarrhea. (6.1)
- Most common Grade 3 or 4 laboratory abnormalities (incidence ≥2%) are increased ALT, increased AST, decreased neutrophil count, and decreased hemoglobin. (6.1)

To report SUSPECTED ADVERSE REACTIONS, contact US WorldMeds at 1-877-IWILFIN or FDA at 1-800-FDA-1088 or www.fda.gov/medwatch

8 USE IN SPECIFIC POPULATIONS

Lactation: Advise not to breastfeed. (8.2)

Renal Impairment: Reduce the dose in patients with estimated Glomerular Filtration Rate (eGFR) <30 mL/min. (2.3, 8.5, 12.3)

FULL PRESCRIBING INFORMATION

1 INDICATIONS AND USAGE

IWILFIN (eflornithine) is indicated to reduce the risk of relapse in adult and pediatric patients with high-risk neuroblastoma (HRNB) who have demonstrated at least a partial response to prior multiagent, multimodality therapy including anti-GD2 immunotherapy.

2 DOSAGE AND ADMINISTRATION

2.1 Recommended Testing Before Initiating IWILFIN

Prior to initiating IWILFIN, perform complete blood count, liver function tests, and baseline audiogram [see Warnings and Precautions (5.1-5.3)].

2.2 Recommended Dosage of IWILFIN

The recommended IWILFIN dosage, based on body surface area (BSA), is provided in Table 1.

Administer IWILFIN orally twice daily for two years or until recurrence of disease or unacceptable toxicity.

Recalculate the BSA dosage every 3 months during treatment with IWILFIN.

Table 1: Recommended Dose
Body Surface Area (m^2) | Dosage
>1.5 | 768 mg (four tablets) orally twice a day
0.75 to 1.5 | 576 mg (three tablets) orally twice a day
0.5 to < 0.75 | 384 mg (two tablets) orally twice a day
0.25 to < 0.5 | 192 mg (one tablet) orally twice a day

2.3 Dosage Recommendations for Renal Impairment

For the treatment of patients with severe renal impairment (eGFR <30 mL/min), reduce the recommended dose of IWILFIN by 50% as described in Table 2 [see Use in Specific Populations (8.5), Clinical Pharmacology (12.3)].

Table 2: IWILFIN Dose Recommendations for Severely Renally Impaired Patients
Body Surface Area (m^2) | Recommended Dosage for Patients with Severe Renal Impairment (eGFR <30 mL/min)
>1.5 | 384 mg (two tablets) orally twice a day
0.75 to 1.5 | 384 mg (two tablets) in the morning and 192 mg (one tablet) in the evening
0.5 to < 0.75 | 192 mg (one tablet) orally twice a day
0.25 to < 0.5 | 192 mg (one tablet) once a day

2.4 Dosage Modifications for Adverse Reactions

The recommended dose reductions for adverse reactions are provided in Table 3.

Table 3: Recommended IWILFIN Dose Reductions for Toxicity Management
Current Dose | Reduced Dose
768 mg (four tablets) orally twice a day | 576 mg (three tablets) orally twice a day
576 mg (three tablets) orally twice a day | 384 mg (two tablets) orally twice a day
384 mg (two tablets) orally twice a day | 192 mg (one tablet) orally twice a day
192 mg (one tablet) orally twice a day | 192 mg (one tablet) orally once daily

If subsequent adverse reactions occur, continue dose reduction until reaching the minimum dose of one 192 mg tablet once per day. Permanently discontinue IWILFIN if the patient is unable to tolerate the minimum dose of 192 mg once daily.

The recommended dosage modifications of IWILFIN for the management of adverse reactions are provided in Table 4.

Table 4: Recommended IWILFIN Dosage Modifications for Adverse Reactions
Adverse Reaction | Severity [Severity as defined by National Cancer Institute Common Terminology Criteria for Adverse Events (NCI CTCAE) version 4.03] | Dosage Modification
Myelosuppression [see Warnings and Precautions (5.1)]
Neutrophil count decreased | <500/mm^3 | Withhold IWILFIN until recovery to ≥500/mm^3.; - If recovered within 7 days, resume IWILFIN at the same dose. - If recovered after 7 days, resume IWILFIN at the next reduced dose level.
Platelet count decreased | <25,000/mm^3 | Withhold IWILFIN until recovery to ≥25,000/mm^3.; - If recovered within 7 days, resume IWILFIN at the same dose. - If recovered between 7 and 14 days, resume IWILFIN at the next reduced dose level.; If not recovered within 14 days, permanently discontinue IWILFIN.
Anemia | <8g/dL | Withhold IWILFIN until recovery to ≥8g/dL.; - Resume IWILFIN at the same dose.; If anemia recurs (<8g/dL); - Withhold IWILFIN until recovery to ≥8g/dL. - Resume IWILFIN at the next reduced dose level.
Hepatotoxicity [see Warnings and Precautions (5.2)]
Aspartate aminotransferase increased or Alanine aminotransferase increased | AST or ALT ≥10 × ULN | Withhold IWILFIN until recovery to <10 × ULN.; - If recovered within 7 days, resume IWILFIN at the same dose. - If recovered after 7 days, resume IWILFIN at the next reduced dose level.
Hearing Loss [see Warnings and Precautions (5.3)]
Hearing loss | Clinically concerning new or worsening hearing loss compared to IWILFIN baseline audiogram | Continue dosing with IWILFIN and repeat audiogram in 3 weeks.; - If improved, continue IWILFIN at the same dose. - If clinically concerning changes persist, hold IWILFIN for up to 30 days and repeat audiogram.; If stable or improved, resume IWILFIN at the next reduced dose level.
Other Adverse Reactions [see Adverse Reactions (6.1)]
Nausea, vomiting, or diarrhea | Grade 3 | If symptoms respond to supportive treatment (e.g., anti-emetic, anti-diarrheal), continue dosing with IWILFIN at the same dose. If symptoms do not respond to treatment,; - Withhold IWILFIN until recovery to ≤ Grade 2. - Resume IWILFIN at the next reduced dose level.
Other adverse reactions | Grade 3 or 4 | Withhold IWILFIN until recovery to ≤ Grade 2.; - Resume IWILFIN at the next reduced dose level.
Other adverse reactions | Recurrent Grade 4 | Permanently discontinue IWILFIN.

2.5 Administration, Crushed Preparation, and Missed Dose Instructions

Administration

- Administer IWILFIN orally twice daily, with or without food, for two years or until recurrence of disease or unacceptable toxicity [see Clinical Pharmacology (12.3)].
- IWILFIN tablets can be swallowed whole, chewed, or crushed.

Crushed Preparation

- For patients who have difficulty swallowing tablets, IWILFIN can be chewed, or crushed then mixed with two tablespoons of soft food or liquid.
- Visually confirm the entire contents are consumed. If any crushed tablet particles remain in the container, mix with an additional small volume (e.g., no more than one ounce, 30 mL) of soft food or liquid.
- Discard crushed tablet preparation after one hour.

Missed Dose

- A missed dose of IWILFIN should be administered as soon as possible. If the next dose is due within 7 hours, the missed dose should be skipped.
- If vomiting occurs after taking IWILFIN, an additional dose should not be administered. Continue with the next scheduled dose.

3 DOSAGE FORMS AND STRENGTHS

Tablets: 192 mg eflornithine, white to off-white, round, imprinted with "EFL" on one side and "192" on the other side.

4 CONTRAINDICATIONS

None.

5 WARNINGS AND PRECAUTIONS

5.1 Myelosuppression

IWILFIN can cause myelosuppression. In the pooled safety population [see Adverse Reactions (6.1)], Grade 3 or 4 neutropenia occurred in 4.2% of patients. Febrile neutropenia occurred in 0.6% of patients. Bone marrow failure occurred in 1 patient. Grade 3 or 4 thrombocytopenia occurred in 1.4% of patients. Grade 3 anemia occurred in 3.3% of patients.

Monitor blood counts including neutrophil count, platelet count, and hemoglobin level prior to administration of IWILFIN and periodically during treatment. Withhold, reduce the dose, or permanently discontinue IWILFIN based on severity [see Dosage and Administration (2.4)].

5.2 Hepatotoxicity

IWILFIN can cause hepatotoxicity. In the pooled safety population [see Adverse Reactions (6.1)], Grade 3 or 4 events of increased alanine aminotransferase (ALT) occurred in 11% of patients. Grade 3 or 4 events of increased aspartate aminotransferase (AST) occurred in 6% of patients. Grade 3 or 4 events of increased bilirubin occurred in 0.3% of patients. Increased ALT/AST leading to dose interruption or reduction occurred in 2.5% of patients. IWILFIN was discontinued due to increased ALT/AST in 0.6% of patients.

Perform liver function tests (ALT, AST, and total bilirubin) prior to the start of IWILFIN, every month for the first six months of treatment, then once every 3 months or as clinically indicated, with more frequent testing in patients who develop transaminase or bilirubin elevations. Withhold and reduce the dose or permanently discontinue IWILFIN based on severity [see Dosage and Administration (2.4) and Adverse Reactions (6.1)].

5.3 Hearing Loss

IWILFIN can cause hearing loss. In the pooled safety population [see Adverse Reactions (6.1)], 81% of patients had an abnormal audiogram at baseline. New or worsening hearing loss occurred in 13% of patients who received IWILFIN; hearing loss worsened from baseline to Grade 3 or 4 in 12% of patients. Tinnitus occurred in 1 patient. Hearing loss leading to dose interruption or reduction occurred in 4% of patients. New or worsening hearing loss requiring new use of hearing aids occurred in 7% of patients. IWILFIN was discontinued due to hearing loss in 1.4% of patients. Among all patients with new or worsening hearing loss during IWILFIN treatment, the hearing loss resolved to baseline in 9% of patients. Among 18 patients who experienced new or worsening hearing loss and had dose modifications, 67% (N=12) improved or resolved to baseline.

Perform audiogram prior to initiation of therapy and at 6 month intervals, or as clinically indicated, to monitor for potential hearing loss. Withhold and reduce the dose or permanently discontinue IWILFIN based on severity [see Dosage and Administration (2.1, 2.4)].

5.4 Embryo-Fetal Toxicity

Based on findings from animal studies and its mechanism of action, IWILFIN can cause fetal harm when administered to a pregnant woman. In animal reproduction studies, oral administration of eflornithine to pregnant rats and rabbits during the period of organogenesis resulted in embryolethality at doses equivalent to the recommended human dose.

Advise pregnant women and females of reproductive potential of the potential risk to a fetus. Advise females of reproductive potential to use effective contraception during treatment with IWILFIN and for 1 week after the last dose. Advise males with female partners of reproductive potential to use effective contraception during treatment with IWILFIN and for 1 week after the last dose [see Use in Specific Populations (8.1, 8.3)].

6 ADVERSE REACTIONS

The following clinically significant adverse reactions are described elsewhere in the labeling:

- Myelosuppression [see Warnings and Precautions (5.1)]
- Hepatotoxicity [see Warnings and Precautions (5.2)]
- Hearing Loss [see Warnings and Precautions (5.3)]

6.1 Clinical Trials Experience

Because clinical trials are conducted under widely varying conditions, adverse reaction rates observed in the clinical trials of a drug cannot be directly compared to rates in the clinical trials of another drug and may not reflect rates observed in clinical practice.

The pooled safety population described in the WARNINGS AND PRECAUTIONS reflect exposure to IWILFIN as a single agent, taken orally at doses ranging from 192 - 768 mg twice daily, based on body surface area (BSA), until disease progression, unacceptable toxicity, or for a maximum of 2 years in patients who demonstrated at least a partial response to prior multiagent, multimodality therapy for newly diagnosed or relapsed/refractory high-risk neuroblastoma in Study 3b (n=101; NCT02395666) and Study 14 (n=259; NCT02679144). Among 360 patients who received IWILFIN, 84% were exposed for 6 months or longer and 73% were exposed for greater than one year. In this pooled safety population, the most common (≥5%) adverse reactions were hearing loss (11%), otitis media (10%), pyrexia (7%), pneumonia (5%), and diarrhea (5%). The most common (≥2%) Grade 3 or 4 laboratory abnormalities were increased ALT (11%), increased AST (6%), decreased neutrophils (4.2%), and decreased hemoglobin (3.3%).

Study 3b

The safety of IWILFIN was evaluated in Study 3b [see Clinical Studies (14.1)]. Eligible patients were pediatric patients with high-risk neuroblastoma (HRNB) who demonstrated at least a partial response to prior multiagent, multimodality therapy including induction, consolidation, and anti-GD2 immunotherapy. Patients received IWILFIN as a single agent taken orally at doses ranging from 192 - 768 mg twice daily, based on body surface area (BSA), until disease progression, unacceptable toxicity, or for a maximum of 2 years (N=85). Among patients who received IWILFIN, 93% were exposed for 6 months or longer and 89% were exposed for greater than one year.

The median age of patients who received IWILFIN was 4 years (range: 1 to 17); 59% male; 85% White, 7% Black, 1% Asian, 8% Hispanic or Latino; 87% had International Neuroblastoma Staging System Stage 4 disease; 47% had neuroblastoma with known MYCN-amplification.

Serious adverse reactions occurred in 12% of patients who received IWILFIN. Serious adverse reactions in >1 patient included skin infection (3 patients).

Permanent discontinuation of IWILFIN due to an adverse reaction occurred in 11% of patients. Adverse reactions which resulted in permanent discontinuation of IWILFIN in >1 patient included hearing loss.

Dose reductions of IWILFIN due to an adverse reaction occurred in 8% of patients. Adverse reactions which required dose reductions in >1 patient included hearing loss.

The most common (≥5%) adverse reactions, including laboratory abnormalities, were otitis media, diarrhea, cough, sinusitis, pneumonia, upper respiratory tract infection, conjunctivitis, vomiting, pyrexia, allergic rhinitis, decreased neutrophils, increased ALT, increased AST, hearing loss, skin infection, and urinary tract infection.

Table 5 summarizes the adverse reactions in Study 3b.

Table 5: Adverse Reactions (≥5%) in Patients with HRNB Who Received IWILFIN in Study 3b
Adverse Reaction [Severity as defined by CTCAE Version 4.03.] | IWILFIN (n=85)
Adverse Reaction [Severity as defined by CTCAE Version 4.03.] | All Grades [Grade 1 adverse events were not comprehensively collected in Study 3b.] , [No Grade 4 or 5 events were reported.] (%) | Grade 3 (%)
Infections
Otitis media | 32 | 2.4
Sinusitis | 13 | 0
Pneumonia | 12 | 1.2
Upper respiratory tract infection | 11 | 0
Conjunctivitis | 11 | 0
Skin infection | 7 | 4.7
Urinary tract infection | 6 | 1.2
Gastrointestinal Disorders
Diarrhea [Includes colitis.] | 15 | 3.5
Vomiting | 11 | 1.2
Respiratory Disorders
Cough | 15 | 0
Allergic rhinitis | 11 | 0
General Disorders
Pyrexia | 11 | 1.2
Ear and Labyrinth Disorders
Hearing loss | 7 | 7

Clinically relevant adverse reactions in <5% of patients who received IWILFIN included rash, extremity pain, and alopecia.

Table 6 summarizes the laboratory abnormalities in Study 3b.

Table 6: Select Laboratory Abnormalities (≥1%) in Patients with HRNB Who Received IWILFIN in Study 3b
Laboratory Abnormality [Severity as defined by CTCAE Version 4.03.] | IWILFIN (n=85)
Laboratory Abnormality [Severity as defined by CTCAE Version 4.03.] | All Grades [Grade 1 adverse events were not comprehensively collected in Study 3b.] , [No Grade 5 events occurred.] (%) | Grade 3 or 4 (%)
Chemistry
Increased ALT | 9 | 7 [No Grade 4 events occurred.]
Increased AST | 8 | 6
Increased alkaline phosphatase | 4.7 | 2.4
Decreased potassium | 2.4 | 2.4
Decreased glucose | 2.4 | 1.1
Decreased sodium | 2.4 | 2.4
Increased potassium | 1.2 | 0
Increased glucose | 1.2 | 0
Hematology
Decreased neutrophils | 9 | 8
Decreased hemoglobin | 4.7 | 2.4
Decreased white blood cells | 2.4 | 0
Decreased platelets | 1.2 | 0

8 USE IN SPECIFIC POPULATIONS

8.1 Pregnancy

Risk Summary

Based on findings from animal studies and its mechanism of action [see Clinical Pharmacology (12.1)], IWILFIN can cause fetal harm when administered to a pregnant woman. In animal reproduction studies, oral administration of eflornithine to pregnant rats and rabbits during the period of organogenesis resulted in embryolethality at doses equivalent to the recommended human dose [see Data]. There are no available data on the use of IWILFIN in pregnant women. Advise pregnant women and females of reproductive potential of the potential risk to a fetus.

In the U.S. general population, the estimated background risk of major birth defects and miscarriage in clinically recognized pregnancies is 2% to 4% and 15% to 20%, respectively.

Data

Animal Data

In an embryo-fetal development study, once daily oral administration of 30, 80 or 200 mg/kg/day eflornithine to pregnant rats during the period of organogenesis (gestation day 6 to 7) resulted in reduced fetal body weights and an increase in the incidence of skeletal variations (presence of a 14th rudimentary rib, 14th full rib, 27th presacral vertebrae) at 200 mg/kg/day [approximately 0.8 to 2 times the recommended human dose of 1152 ± 384 mg/m^2/day based on body surface area (BSA)]. In a dose range-finding embryo-fetal development study, pregnant rats receiving oral administration of up to 2000 mg/kg/day eflornithine during the period of organogenesis exhibited increased early resorptions and post-implantation loss beginning at 300 mg/kg/day (approximately 1 to 2 times the recommended human dose of 1152 ± 384 mg/m^2/day based on BSA), with 100% post-implantation loss and no viable fetuses at ≥800 mg/kg/day (approximately ≥3 to 6 times the recommended human dose of 1152 ± 384 mg/m^2/day based on BSA).

In an embryo-fetal development study in rabbits, once daily oral administration of 15, 45 or 135 mg/kg/day eflornithine to pregnant animals during the period of organogenesis (gestation day 7 to 20) resulted in reduced gravid uterine weight accompanied by increased pre-implantation and post-implantation loss, increased early resorptions, and reduced fetal body weights at 135 mg/kg/day (approximately 1 to 2 times the recommended human dose of 1152 ± 384 mg/m^2/day based on BSA). Eflornithine resulted in abortions in one animal at 15 mg/kg/day (approximately 0.1 to 0.2 times the recommended human dose of 1152 ± 384 mg/m^2/day based on BSA) and one animal at 135 mg/kg/day. In a dose range-finding embryo-fetal development study, pregnant rabbits receiving oral administration of up to 500 mg/kg/day eflornithine during the period of organogenesis exhibited 100% post-implantation loss and no viable fetuses at 500 mg/kg/day (approximately 4 to 8 times the recommended human dose of 1152 ± 384 mg/m^2/day based on BSA). There was no clear evidence of eflornithine-related fetal malformations in rats or rabbits.

8.2 Lactation

Risk Summary

There are no data on the presence of eflornithine in human milk, the effects on the breastfed child, or on milk production. Because of the potential for serious adverse reactions in breastfed children, advise women not to breastfeed during treatment with IWILFIN and for 1 week after the last dose.

8.3 Females and Males of Reproductive Potential

Based on animal data and its mechanism of action, IWILFIN can cause fetal harm when administered to a pregnant woman [see Use in Specific Populations (8.1)].

Pregnancy Testing

Verify pregnancy status in females of reproductive potential prior to initiating IWILFIN [see Use in Specific Populations (8.1)].

Contraception

Females

Advise females of reproductive potential to use effective contraception during treatment with IWILFIN and for 1 week after the last dose.

Males

Advise males with female partners of reproductive potential to use effective contraception during treatment with IWILFIN and for 1 week after the last dose.

8.4 Pediatric Use

The safety and effectiveness of IWILFIN have been established to reduce the risk of relapse in pediatric patients with high-risk neuroblastoma (HRNB) who have demonstrated at least a partial response to prior multiagent, multimodality therapy including anti-GD2 immunotherapy. Use of IWILFIN for this indication is supported by evidence from adequate and well-controlled studies in pediatric patients with a median age of 4 years (range: 1 to 17) [see Adverse Reactions (6.1), Clinical Pharmacology (12.3), Clinical Studies (14.1)].

The safety and effectiveness of IWILFIN have not been established in pediatric patients for other indications [see Indications and Usage (1)].

8.5 Renal Impairment

Patients with moderate (eGFR <60 mL/min) and severe (eGFR <30 mL/min) renal impairment have a higher exposure to eflornithine than patients with normal renal function which can increase the risk for toxicity [see Clinical Pharmacology (12.3)]. Reduce the dose in patients with severe renal impairment [see Dosage and Administration (2.3)]. Monitor patients with moderate renal impairment closely for increased adverse reactions including hepatotoxicity, myelosuppression, and hearing loss [see Dosage and Administration (2.4)].

11 DESCRIPTION

IWILFIN is an ornithine decarboxylase inhibitor. The chemical name of eflornithine hydrochloride is 2,5-diamino-2-(difluoromethyl) pentanoic acid hydrochloride hydrate with a molecular formula of C6H12F2N2O2∙HCl∙H2O. Its molecular weight is 236.65g/mol for the salt and hydrate form and 182.17 g/mol for the anhydrous free base form. Eflornithine hydrochloride is a white to off-white powder, freely soluble in water and sparingly soluble in ethanol. The chemical structure of eflornithine hydrochloride is:

IWILFIN is available as a round, white to off-white tablet for oral administration. Each tablet contains 192 mg eflornithine, equivalent to 250 mg of eflornithine hydrochloride, and the following inactive ingredients: 220 mg silicified microcrystalline cellulose, 25 mg partially pregelatinized maize starch, 2.5 mg colloidal silicon dioxide, and 2.5 mg vegetable source magnesium stearate.

12 CLINICAL PHARMACOLOGY

12.1 Mechanism of Action

Eflornithine is an irreversible inhibitor of the enzyme ornithine decarboxylase (ODC), the first and rate-limiting enzyme in the biosynthesis of polyamines and a transcriptional target of MYCN. Polyamines are involved in differentiation and proliferation of mammalian cells and are important for neoplastic transformation. Inhibition of polyamine synthesis by eflornithine restored the balance of the LIN28/Let-7 metabolic pathway, which is involved in regulation of cancer stem cells and glycolytic metabolism, by decreasing expression of the oncogenic drivers MYCN and LIN28B in MYCN-amplified neuroblastoma. In vitro, eflornithine induced senescence and suppressed neurosphere formation in MYCN-amplified and MYCN non-amplified neuroblastoma cells, indicating a cytostatic effect. Treatment with eflornithine prevented or delayed tumor formation in mice injected with limiting dilutions of MYCN-amplified neuroblastoma cells.

12.2 Pharmacodynamics

Eflornithine exposure-response relationships and the time course of pharmacodynamic responses are unknown.

Cardiac Electrophysiology

At the recommended dose, IWILFIN did not result in a large mean increase (i.e., >20 ms) of the QTc interval.

12.3 Pharmacokinetics

Absorption

Following oral administrations of IWILFIN, peak plasma concentrations of eflornithine (Cmax) were achieved (Tmax) 3.5 hours post dosing.

Effect of Food

The Cmax and AUC (area under the concentration-time curve) of eflornithine were not affected by food (high fat and high calories). Administration of crushed tablets in a standard pudding admixture had no effect on eflornithine exposure (Cmax and AUC6h).

Distribution

Eflornithine does not specifically bind to human plasma proteins. Eflornithine volume of distribution (Vz/F) is 24.3 L.

Elimination

Excretion

Terminal plasma elimination half-life of eflornithine is 3.5 hours. Clearance (CL/F) is 5.3 L/h.

Specific Populations

Pharmacokinetic analyses from patients in Study 14 suggested that age (1 year to 19 years), sex, or body surface area (0.4 m^2 to 2 m^2), and mild hepatic impairment (bilirubin ≤ULN and AST>ULN or bilirubin >1 × ULN and any AST) had no clinically meaningful effects on eflornithine exposure.

Renal Impairment

Following oral administration of a single IWILFIN dose of 576 mg, exposure (AUC) of eflornithine was 2-fold higher in adults with moderate renal impairment and 4-fold higher in adults with severe renal impairment when compared to adults with normal renal function.

13 NONCLINICAL TOXICOLOGY

13.1 Carcinogenesis, Mutagenesis, Impairment of Fertility

In a 2-year carcinogenicity study, once daily oral administration of eflornithine to female rats did not result in drug-related neoplasms at doses up to 600 mg/kg/day (10.5 times the human Cmax at the recommended clinical dose of 1152 ± 384 mg/m^2).

Eflornithine was not mutagenic in the in vitro bacterial reverse mutation (Ames) assay.

Dedicated fertility studies were not conducted with eflornithine.

14 CLINICAL STUDIES

The efficacy of IWILFIN is based on an externally controlled trial comparison of Study 3b (investigational arm) and Study ANBL0032 (clinical trial-derived external control arm).

Study 3b

Study 3b (NCT02395666) was a multi-center, open label, non-randomized trial with two cohorts. Eligible patients in one cohort (Stratum 1) were pediatric patients with high-risk neuroblastoma (HRNB) who demonstrated at least a partial response to prior multiagent, multimodality therapy, including induction, consolidation, and anti-GD2 immunotherapy. A total of 105 eligible patients received IWILFIN orally twice daily, dosage based on body surface area (BSA) until disease progression, unacceptable toxicity, or for a maximum of 2 years [see Dosage and Administration (2.1)]. Tumor assessments were performed at 3, 6, 9, 12, 18 months, completion of treatment, and as clinically indicated. Following completion of IWILFIN therapy, patients were followed for a total duration of 7 years. The major efficacy outcome measure was event free survival (EFS), defined as disease progression, relapse, secondary cancer, or death due to any cause. An additional efficacy outcome measure was overall survival (OS), defined as death due to any cause. Study 3b was prospectively designed to compare outcomes to the historical EFS rate from Study ANBL0032 reported in published literature.

External Comparator: ANBL0032

The external control arm was derived from 1,241 patients on the experimental arm of Study ANBL0032, a multi-center, open-label, randomized trial of dinutuximab, granulocyte-macrophage colony-stimulating factor, interleukin-2, and cis-retinoic acid compared to cis-retinoic acid alone in pediatric patients with HRNB previously treated with induction and consolidation therapy who achieved at least a partial response to prior autologous stem cell transplant. Tumor assessments were performed post-immunotherapy at 3, 6, 9, 12, 18, 24, 30, and 36 months, then per standard of care for a total of 10 years.

Externally Controlled Trial

The efficacy population for the comparative analysis of Study 3b and ANBL0032 included patients from both studies who were less than 21 years of age with histologic verification of HRNB and who demonstrated at least a partial response based on imaging, with no evidence of disease in the bone marrow, at the end of immunotherapy, and did not experience an EFS event prior to starting IWILFIN maintenance therapy (for Study 3b), or for at least 30 days from the end of immunotherapy (for ANBL0032). Eligible patients on Study 3b received immunotherapy on ANBL0032 or were treated off study according to the ANBL0032 protocol. Patients who met the criteria for the comparison and had complete data for specified clinical covariates were matched (1:3) using propensity scores; the matched efficacy populations for the primary analysis included 90 patients treated with IWILFIN and 270 control patients from ANBL0032. The demographic characteristics of the primary analysis population (N=360) were 59% male; median age at diagnosis 3 years (range: 0.1 to 20.1); 88% White, 6% Black, 4% Asian, 7% Hispanic. The majority of patients had Stage 4 disease (86%) and MYCN amplification was observed in 44% of tumors. End of immunotherapy responses were complete response (CR; 87%), very good partial response (VGPR; 8%), or partial response (PR; 5%).

In the protocol-specified primary analysis, the EFS hazard ratio (HR) was 0.48 (95% CI: 0.27, 0.85) and OS HR was 0.32 (95% CI: 0.15, 0.70). The Kaplan-Meier plot for the primary analysis of EFS, with shaded bands for each curve representing the point-wise 95% confidence intervals, is shown in Figure 1. Given the uncertainty associated with the externally controlled study design, supplementary analyses in subpopulations or using alternative statistical methods were performed. In these analyses, the EFS HR ranged from 0.43 (95% CI: 0.23, 0.79) to 0.59 (95% CI: 0.28, 1.27), and the OS HR ranged from 0.29 (95% CI: 0.11, 0.72) to 0.45 (95% CI: 0.21, 0.98).

Figure 1: Kaplan-Meier Curve for Event Free Survival for Protocol-Specified Primary Analysis in the Externally Controlled Trial

16 HOW SUPPLIED/STORAGE AND HANDLING

IWILFIN (eflornithine) is available as 192 mg round, white to off-white tablets imprinted with EFL on one side and 192 on the other side; approximately 11 mm in diameter and supplied as follows:

- Bottle of 100 tablets containing desiccant, NDC 78670-150-01

STORAGE AND HANDLING

Store at room temperature, 20°C to 25°C (68°F to77°F), excursions permitted between 15°C to 30°C (59°F to 86°F) [see USP Controlled Room Temperature].

17 PATIENT COUNSELING INFORMATION

Advise the patient to read the FDA-approved patient labeling (Patient Information).

Myelosuppression

Inform patients and caregivers of the risk of bone marrow suppression and to promptly report any signs or symptoms of thrombocytopenia, anemia, or infection [see Warnings and Precautions (5.1)].

Hepatotoxicity

Inform patients and caregivers of the risk of hepatotoxicity and to promptly report any signs or symptoms of hepatotoxicity [see Warnings and Precautions (5.2)].

Hearing Loss

Inform patients and caregivers of the risk of hearing loss, and to promptly report any signs or symptoms of new or worsening hearing loss [see Warnings and Precautions (5.3)].

Embryofetal Toxicity

Inform patients and caregivers that IWILFIN can be harmful to a developing fetus and cause loss of pregnancy [see Warnings and Precautions (5.4)]. Advise females of reproductive potential to use effective contraception during treatment with IWILFIN and for 1 week after the last dose. Advise males with female partners of reproductive potential to use effective contraception during treatment with IWILFIN and for 1 week after the last dose [see Use in Specific Populations (8.3)].

Lactation

Advise women not to breastfeed during treatment with IWILFIN and for 1 week after the last dose [see Use in Specific Populations (8.2)].

US WorldMeds®

Distributed by:
USWM, LLC
4441 Springdale Road
Louisville, KY 40241

©2025. IWILFIN® is a registered trademark of USWM, LLC.

FPI-0026.1

Patient Information
IWILFIN® (I-WILL-fin)
(eflornithine)
tablets

What is IWILFIN?
IWILFIN is a prescription medicine used to reduce the risk of relapse in adults and children with high-risk neuroblastoma (HRNB) who have had at least a partial response to certain prior therapies.

Before you take IWILFIN, tell your healthcare provider about all of your medical conditions, including if you:

- have hearing problems
- are pregnant or plan to become pregnant. IWILFIN can harm your unborn baby. Tell your healthcare provider right away if you become pregnant during treatment with IWILFIN or think you may be pregnant.
  - Females who are able to become pregnant should have a pregnancy test before starting treatment with IWILFIN.
    You should use effective birth control during treatment with IWILFIN and for 1 week after the last dose.
  - Males who have female partners who are able to become pregnant should use effective birth control during treatment with IWILFIN and for 1 week after the last dose.
- are breastfeeding or plan to breastfeed. It is not known if IWILFIN passes into your breast milk. Do not breastfeed during treatment with IWILFIN and for 1 week after the last dose.

Tell your healthcare provider about all the medicines you take, including prescription and over-the-counter medicines, vitamins, and herbal supplements.

How should I take IWILFIN?

- Take IWILFIN exactly as your healthcare provider tells you to take it.
- Take IWILFIN 2 times a day with or without food.
- Swallow tablets whole. If you cannot swallow tablets whole, IWILFIN can be chewed, or crushed then mixed with soft food or liquid. If you are crushing IWILFIN tablets:
  - IWILFIN can be crushed then mixed with 2 tablespoons of soft food or liquid.
  - Eat the entire mixture.
  - If any crushed tablet pieces remain, mix with another small amount (about 2 tablespoons) of soft food or liquid.
  - Take all of the mixture within 1 hour of mixing. Throw away any mixture left after 1 hour.
- If you miss a dose of IWILFIN, take it as soon as you remember. If it is within 7 hours of your next scheduled dose, skip the missed dose and take your next dose at your regular time.
- If you vomit after taking a dose, do not take an extra dose. Take your next dose at your regular time.

What are the possible side effects of IWILFIN?
IWILFIN may cause serious side effects, including:

- Low blood cell counts. IWILFIN can cause low blood cell counts and failure of your bone marrow to make enough platelets, red blood cells, or white blood cells. Your healthcare provider will monitor your blood cell counts before starting and during treatment with IWILFIN. Tell your healthcare provider right away if you develop symptoms of low blood cell counts, including:

- fever (temperature 100.4°F or higher)
- easy bruising or bleeding
- blood in your urine or stools

- feeling unusually tired or weak
- shortness of breath
- chills or shivering

- Liver problems. Your healthcare provider will do blood tests before starting, every month for the first 6 months, and regularly during treatment with IWILFIN to check your liver. Tell your healthcare provider if you develop symptoms of liver problems, including:

- your skin or the white part of your eyes turns yellow (jaundice)
- dark or "tea-colored" urine
- light-colored stools (bowel movements)

- nausea or vomiting
- easy bruising or bleeding
- loss of appetite
- pain, aching, or tenderness on the right side of your stomach-area (abdomen)

- New or worsening hearing loss. Hearing loss is common during treatment with IWILFIN and can also be serious. Your healthcare provider will check your hearing before you start and during treatment with IWILFIN. Some people have needed to use hearing aids. Tell your healthcare provider right way if you get ringing in your ears or any new or worsening hearing loss.

The most common side effects of IWILFIN include:

- ear infection
- diarrhea
- cough
- sinus infection
- pneumonia
- upper respiratory tract infection

- red and swollen eyes (pink eye)
- vomiting
- stuffy, runny, itchy nose or sneezing (allergic rhinitis)
- fever
- skin infection
- urinary tract infection

These are not all the possible side effects of IWILFIN.
Call your doctor for medical advice about side effects. You may report side effects to FDA at 1-800-FDA-1088.

How should I store IWILFIN?

- Store IWILFIN at room temperature between 68°F to 77°F (20°C to 25°C).

Keep IWILFIN and all medicines out of the reach of children.

General information about the safe and effective use of IWILFIN:
Medicines are sometimes prescribed for purposes other than those listed in the Patient Information leaflet. Do not use IWILFIN for a condition for which it was not prescribed. Do not give IWILFIN to other people, even if they have the same symptoms you have. It may harm them. You can ask your healthcare provider or pharmacist for information about IWILFIN that is written for health professionals.

What are the ingredients in IWILFIN?
Active ingredient: eflornithine
Inactive ingredients: silicified microcrystalline cellulose, partially pregelatinized maize starch, colloidal silicon dioxide, and vegetable source magnesium stearate.
Distributed by:
USWM, LLC 4441 Springdale Road Louisville, KY 40241
©2025. IWILFIN® is a registered trademark of USWM, LLC.
For more information, go to www.IWILFIN.com or call 1-877-IWILFIN.

This Patient Information has been approved by the U.S. Food and Drug Administration

Issued: 12/2023

PRINCIPAL DISPLAY PANEL - 192 mg Bottle Carton

Rx only

NDC 78670-150-01

iwilfin™
(eflornithine) tablets

192 mg

Keep the bottle tightly closed.

100 tablets

US WorldMeds®